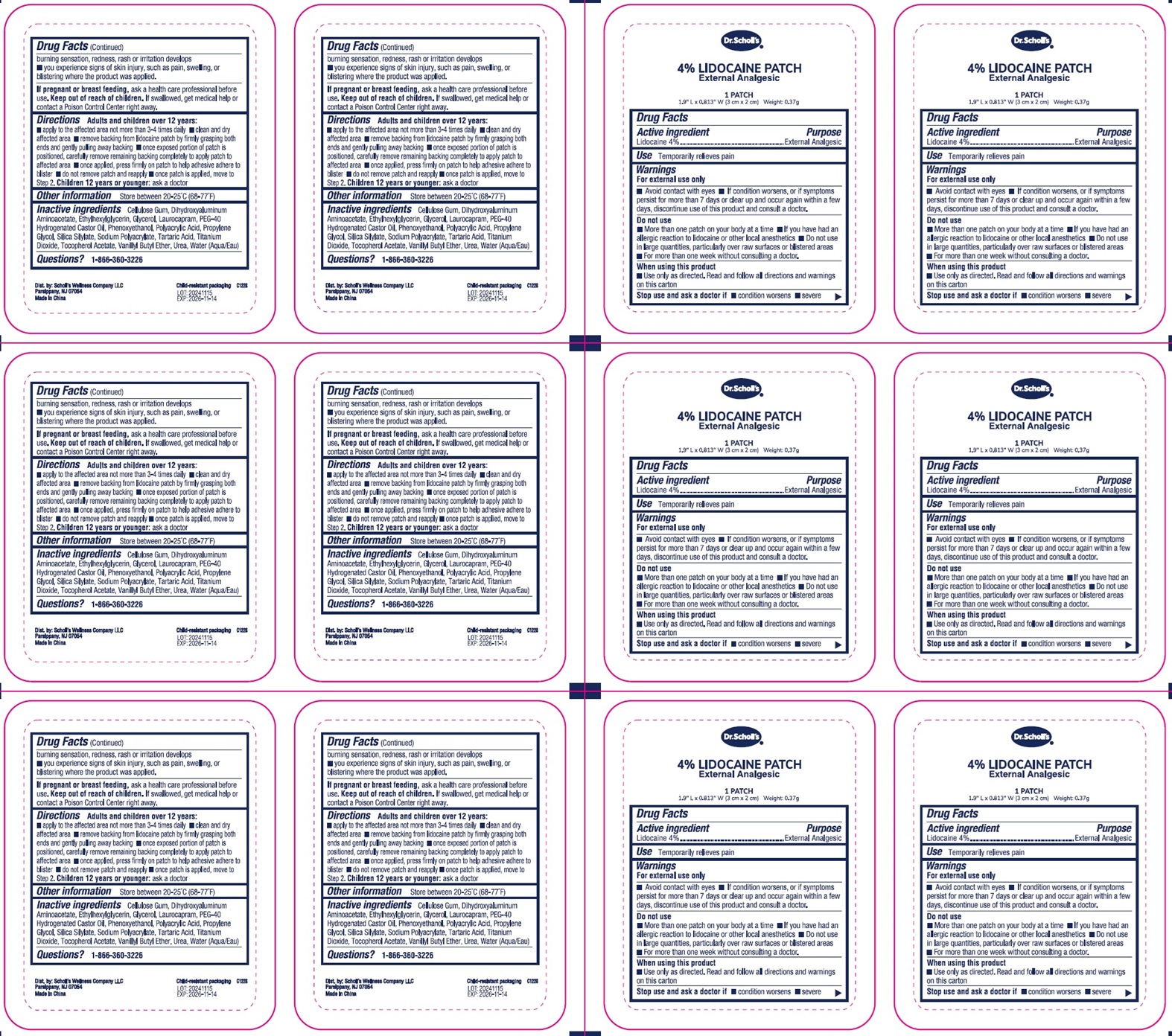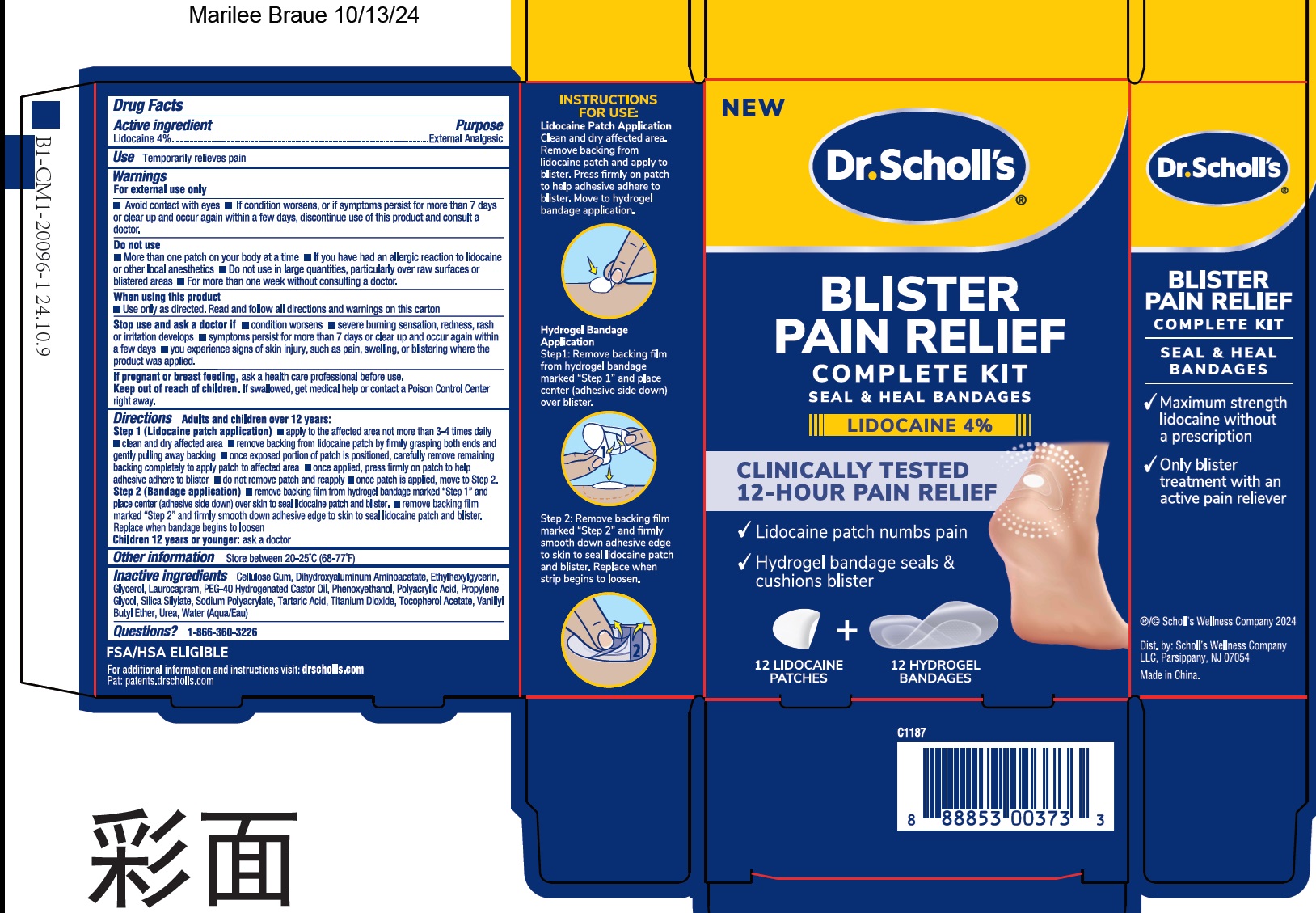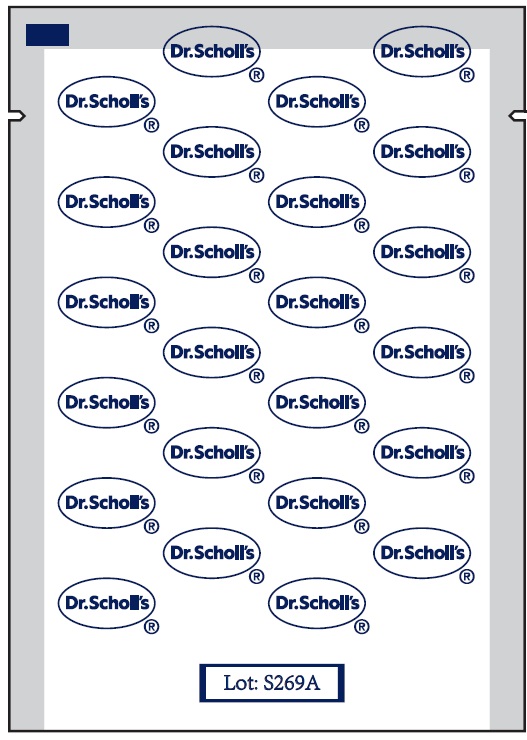 DRUG LABEL: Dr. Scholls Blister Pain Relief Complete
NDC: 73469-0488 | Form: KIT | Route: TOPICAL
Manufacturer: Scholl's Wellness Company LLC
Category: otc | Type: HUMAN OTC DRUG LABEL
Date: 20241218

ACTIVE INGREDIENTS: LIDOCAINE 40 mg/1 g
INACTIVE INGREDIENTS: CELLULOSE GUM; DIHYDROXYALUMINUM AMINOACETATE; ETHYLHEXYLGLYCERIN; GLYCERIN; LAUROCAPRAM; POLYOXYL 40 HYDROGENATED CASTOR OIL; PHENOXYETHANOL; PROPYLENE GLYCOL; TARTARIC ACID; TITANIUM DIOXIDE; .ALPHA.-TOCOPHEROL ACETATE; VANILLYL BUTYL ETHER; UREA; WATER

Dr. Scholl's Blister Pain Relief Complete Kit

Active ingredient

Lidocaine 4%

Purpose

External Analgesic

Use

Temporarily relieves pain

Warnings

For external use only

- Avoid contact with eyes
- If condition worsens, or if symptoms persist for more than 7 days or clear up and occur again within a few days, discontinue use of this product and consult a doctor.

Do not use

- More than one patch on your body at a time
- If you have had an allergic reaction to lidocaine or other local anesthetics
- Do not use in large quantities, particularly over raw surfaces or blistered areas
- For more than one week without consulting a doctor.

When using this product

- Use only as directed. Read and follow all directions and warnings on this carton

Stop use and ask a doctor if

- condition worsens
- severe burning sensation, redness, rash or irritation develops
- symptoms persist for more than 7 days or clear up and occur again within a few days
- you experience signs of skin injury, such as pain, swelling, or blistering where the product was applied.

If pregnant or breast-feeding,

ask a health care professional before use.

Keep out of reach of children.

If swallowed, get medical help or contact a Poison Control Center right away.

Directions

Adults and children over 12 years:

Step 1 (Lidocaine patch application) • apply to the affected area not more than 3-4 times daily

- clean and dry affected area
- remove backing from lidocaine patch by firmly grasping both ends and gently pulling away backing
- once exposed portion of patch is positioned, carefully remove remaining backing completely to apply patch to affected area
- once applied, press firmly on patch to help adhesive adhere to blister
- do not remove patch and reapply
- once patch is applied, move to Step 2.

Step 2 (Bandage application) •remove backing film from hydrogel bandage marked "Step 1" and place center (adhesive side down) over skin to seal lidocaine patch and blister.

- remove backing film marked "Step 2" and firmly smooth down adhesive edge to skin to seal lidocaine patch and blister. Replace when bandage begins to loosen

children 12 years or younger: ask a doctor

Other information

Store between 20-25°C (68-77°F)

Inactive ingredients

Cellulose Gum, Dihydroxyaluminum Aminoacetate, Ethylhexylglycerin, Glycerol, Laurocapram, PEG-40 Hydrogenated Castor Oil, Phenoxyethanol, Polyacrylic Acid, Propylene Glycol, Silica Silylate, Sodium Polyacrylate, Tartaric Acid, Titanium Dioxide, Tocopherol Acetate, Vanillyl Butyl Ether, Urea, Water (Aqua)

Questions?

1-866-360-3226